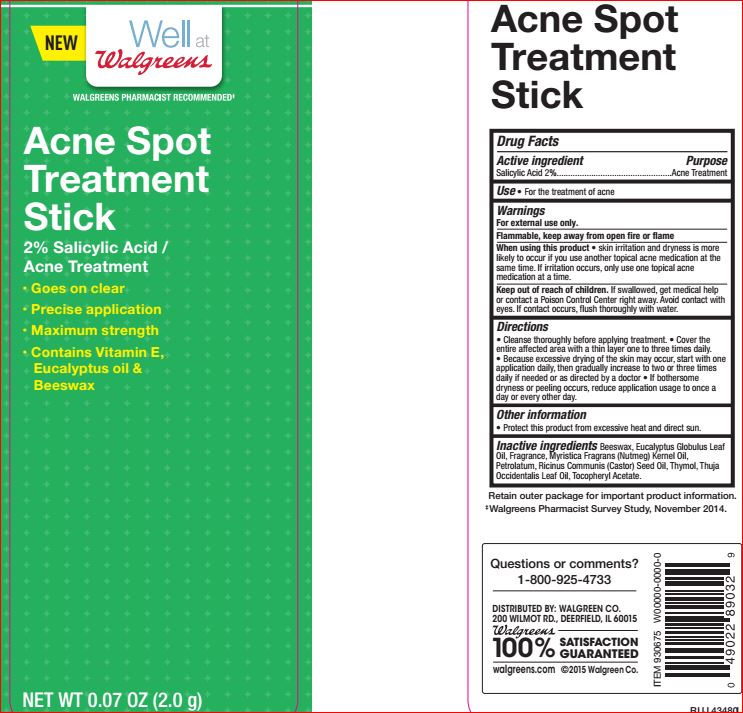 DRUG LABEL: Acne Spot Treatment
NDC: 0363-1115 | Form: STICK
Manufacturer: Walgreens
Category: otc | Type: HUMAN OTC DRUG LABEL
Date: 20180219

ACTIVE INGREDIENTS: Salicylic Acid 2 g/100 g
INACTIVE INGREDIENTS: YELLOW WAX; EUCALYPTUS OIL; NUTMEG OIL; Petrolatum; CASTOR OIL; Thymol; CEDAR LEAF OIL; .ALPHA.-TOCOPHEROL ACETATE

Frug Facts

Active ingredients Purpose

Salicylic Acid….2% Acne Treatment

Uses

For the treatment of acne

Warnings For external use only Flammable. Keep away from fire or flame.

When using this product skin irritation and dryness is more likely occur if you use another topical acne medication at the same time. If irritation occurs, only use one topical acne medication at a time.

Directions
Cleanse thoroughly before applying treatment
Cover the entire affected area with a thin layer one to three times daily.
Because of excessive drying of the skin may occurs, start with one application daily, then gradually increase to two or three times daily if needed or as directed by a doctor.
If bothersome dryness or peeling occurs, reduce application usage to once a day or every other day.

Inactive ingredients

Beeswax
Eucalyptus Globulus Leaf Oil
Fragrance
Myristica Fragrans (Nutmeg) Kernel Oil
Petrolatum
Ricinus Communis (Castor) Seed Oil
Thymol
Thuja Occidentalis Leaf Oil
Tocopheryl Acetate